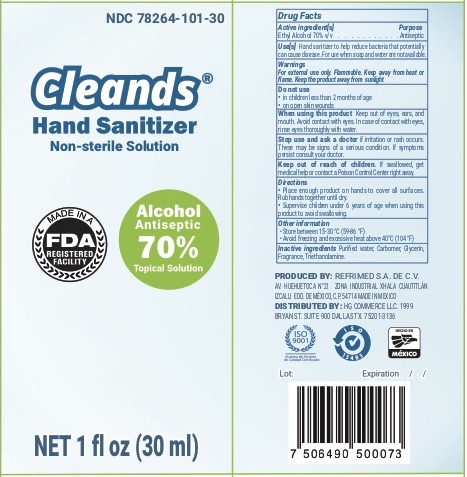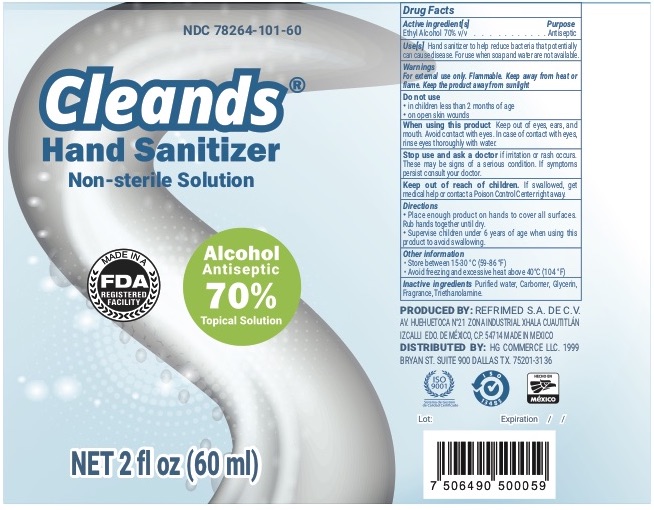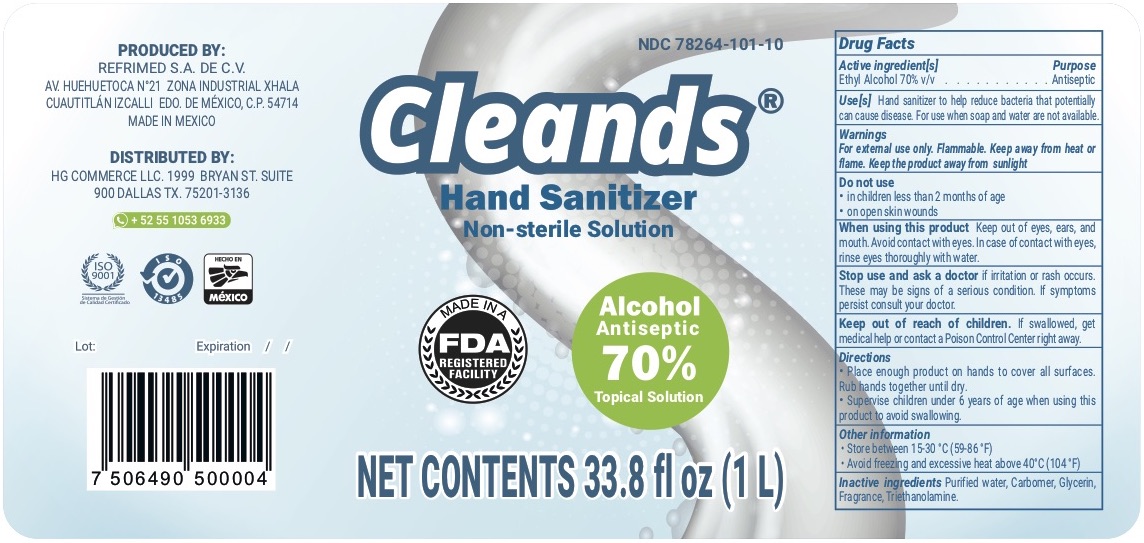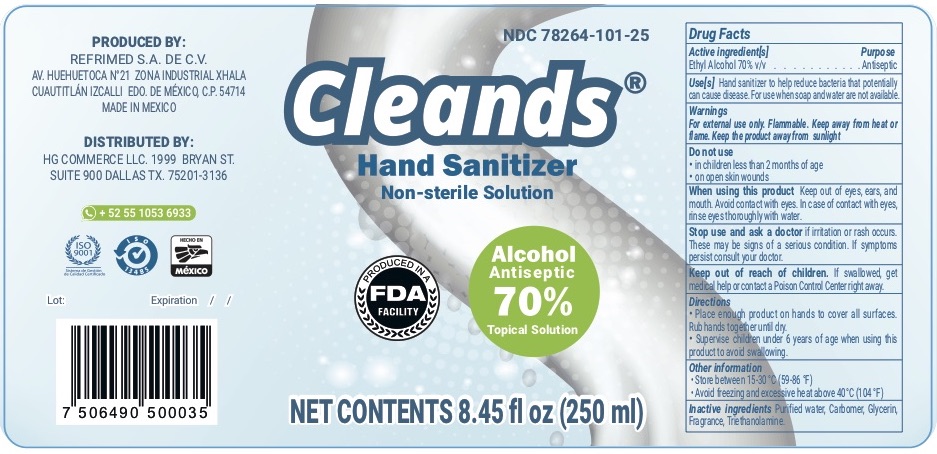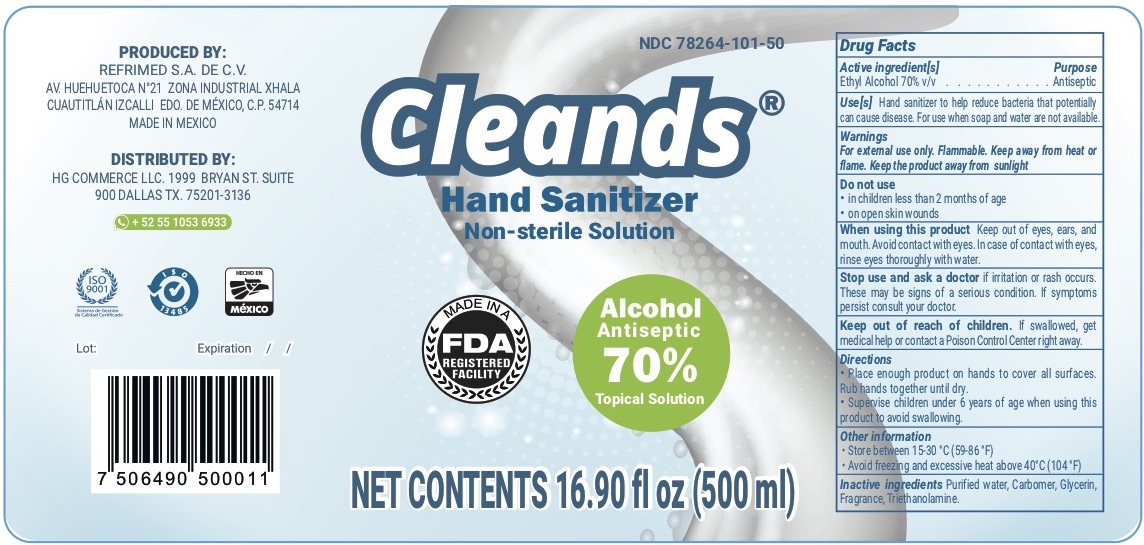 DRUG LABEL: Cleands Hand Sanitizer
NDC: 78264-101 | Form: GEL
Manufacturer: Refrimed, S.A. de C.V.
Category: otc | Type: HUMAN OTC DRUG LABEL
Date: 20200617

ACTIVE INGREDIENTS: ALCOHOL 70 mL/100 mL
INACTIVE INGREDIENTS: CARBOMER HOMOPOLYMER, UNSPECIFIED TYPE; GLYCERIN; WATER; TROLAMINE

Cleands® Hand Sanitizer

Cleands® Hand Sanitizer

Drug Facts

Active ingredient

Alcohol 70% v/v

Purpose

Antiseptic

Use

Hand Sanitizer to help reduce bacteria that potentially can cause disease. For use when soap and water are not available.

Warnings

For external use only. Flammable. Keep away from heat or flame.

Keep the product away from sunlight.

Do not use

• in children less than 2 months of age

• on open skin wounds

When using this product keep out of eyes, ears, and mouth. In case of contact with eyes, rinse eyes thoroughly with water.

Stop use and ask a doctor if irritation or rash occurs. These may be signs of a serious condition. If symptoms persist call your doctor.

Keep out of reach of children. If swallowed, get medical help or contact a Poison Control Center right away.

Directions

• Place enough product on hands to cover all surfaces. Rub hands together until dry.

• Supervise children under 6 years of age when using this product to avoid swallowing.

Inactive ingredients

Purified water, Carbomer,Glycerine, Fragrance, Triethanolamine

Other information

- Other information • Store between 15-30C (59-86F)
- Avoid freezing and excessive heat above 40C (104F)